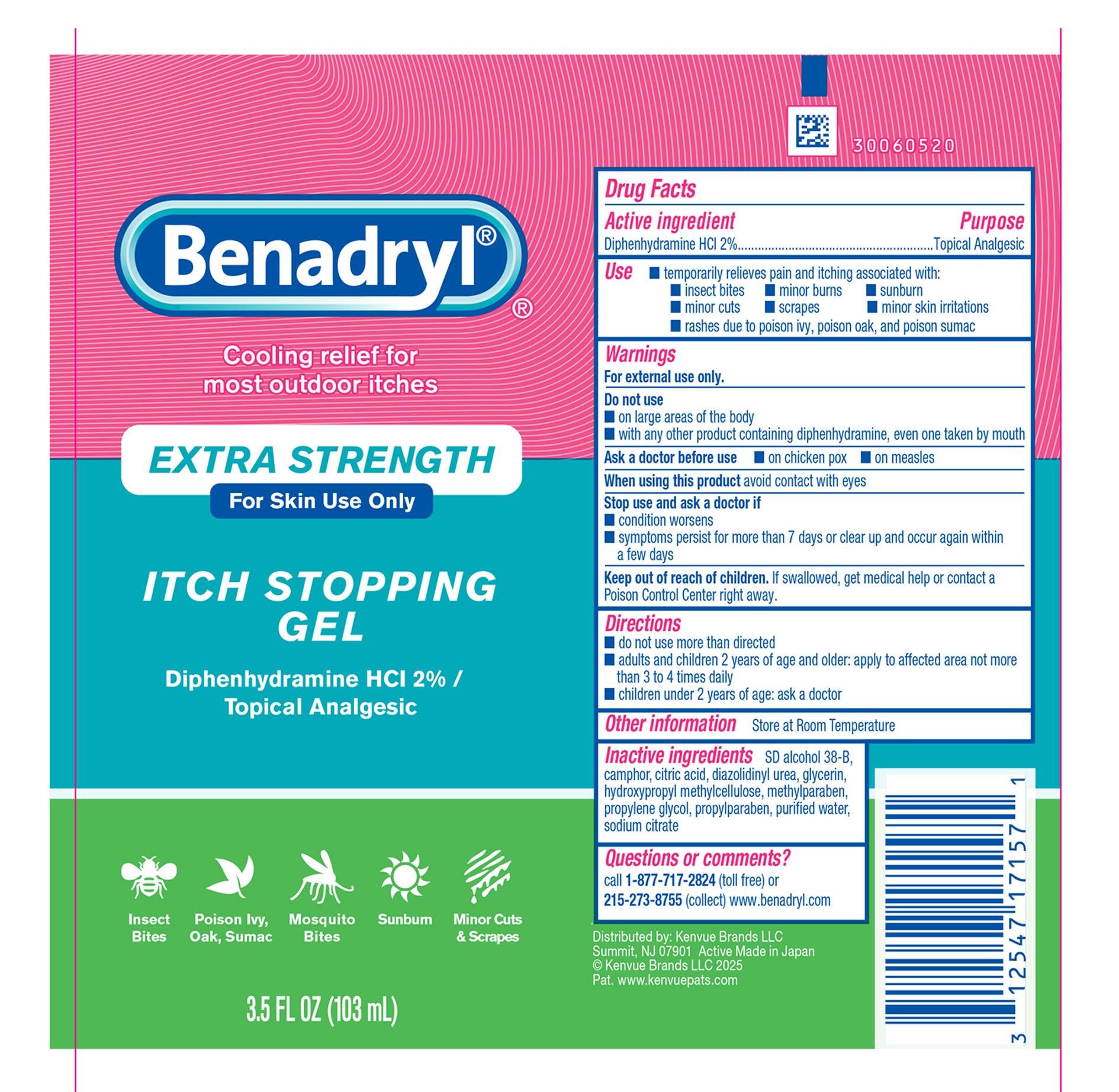 DRUG LABEL: Benadryl Extra Strength Itch Stopping
NDC: 69968-0242 | Form: GEL
Manufacturer: Kenvue Brands LLC
Category: otc | Type: HUMAN OTC DRUG LABEL
Date: 20250424

ACTIVE INGREDIENTS: DIPHENHYDRAMINE HYDROCHLORIDE 20 mg/1 mL
INACTIVE INGREDIENTS: ALCOHOL; CAMPHOR (SYNTHETIC); CITRIC ACID MONOHYDRATE; DIAZOLIDINYL UREA; GLYCERIN; HYPROMELLOSE, UNSPECIFIED; METHYLPARABEN; PROPYLENE GLYCOL; PROPYLPARABEN; WATER; SODIUM CITRATE, UNSPECIFIED FORM

Benadryl® EXTRA STRENGTH ITCH STOPPING GEL

Drug Facts

Active ingredient

Diphenhydramine HCl 2%

Purpose

Topical Analgesic

Use

- temporarily relieves pain and itching associated with:
  - insect bites
  - minor burns
  - sunburn
  - minor cuts
  - scrapes
  - minor skin irritations
  - rashes due to poison ivy, poison oak, and poison sumac

Warnings

For external use only.

Do not use

- on large areas of the body
- with any other product containing diphenhydramine, even one taken by mouth

Ask a doctor before use

- on chicken pox
- on measles

When using this product avoid contact with eyes

Stop use and ask a doctor if

- condition worsens
- symptoms persist for more than 7 days or clear up and occur again within a few days

Keep out of reach of children. If swallowed, get medical help or contact a Poison Control Center right away.

Directions

- do not use more than directed
- adults and children 2 years of age and older: apply to affected area not more than 3 to 4 times daily
- children under 2 years of age: ask a doctor

Other information

Store at Room Temperature

Inactive ingredients

SD alcohol 38-B, camphor, citric acid, diazolidinyl urea, glycerin, hydroxypropyl methylcellulose, methylparaben, propylene glycol, propylparaben, purified water, sodium citrate

Questions or comments?

call 1-877-717-2824 (toll free) or 215-273-8755 (collect) www.benadryl.com

Distributed by:

Kenvue Brands LLC
Summit, NJ 07901

PRINCIPAL DISPLAY PANEL - 103 mL Tube Label

Benadryl®

®

Cooling relief for

most outdoor itches

EXTRA STRENGTH

For Skin Use Only

ITCH STOPPING

GEL

Diphenhydramine HCl 2% /

Topical Analgesic

Insect Bites | Poison Ivy, Oak, Sumac | Mosquito Bites | Sunburn | Minor Cuts & Scrapes

3.5 FL OZ (103 mL)